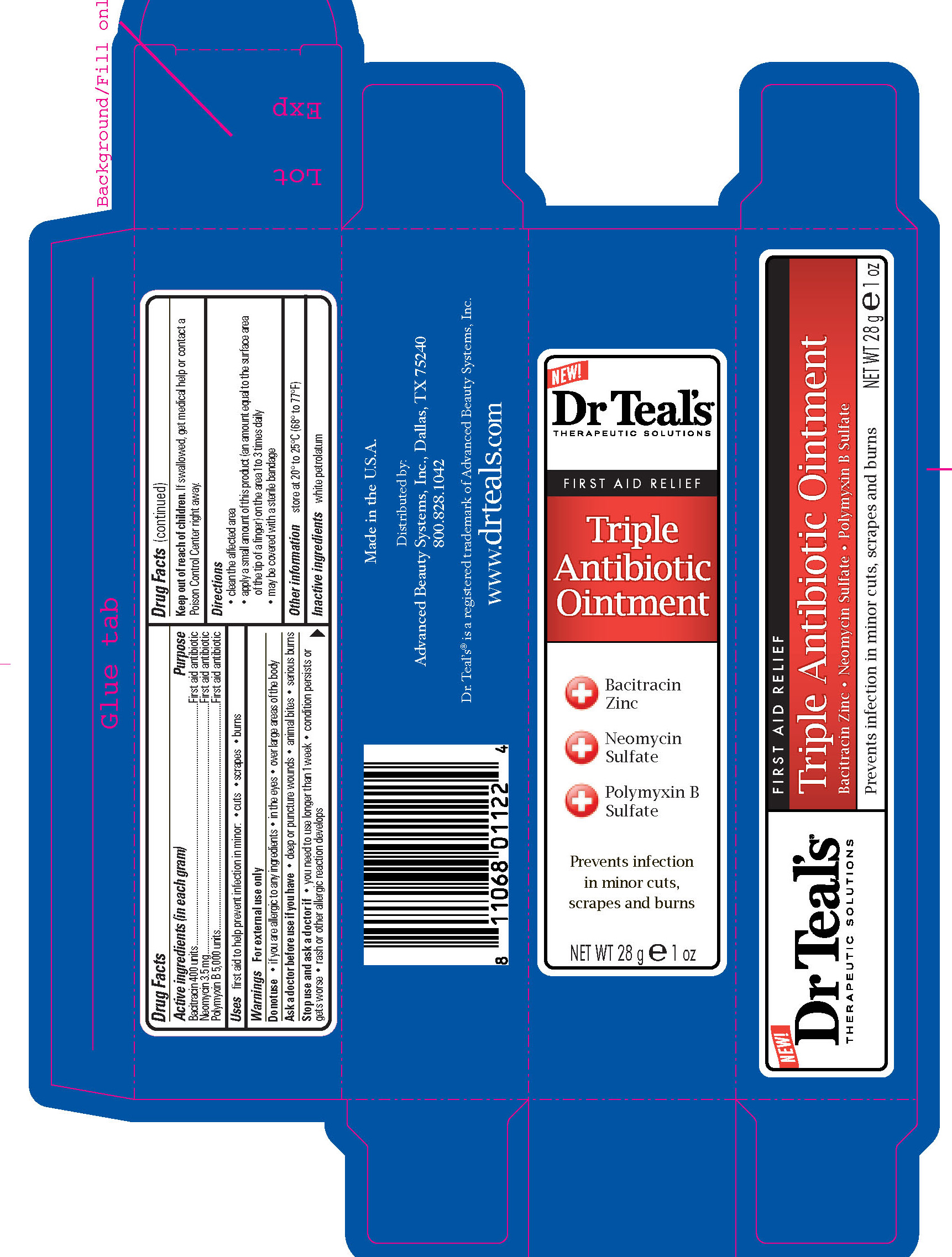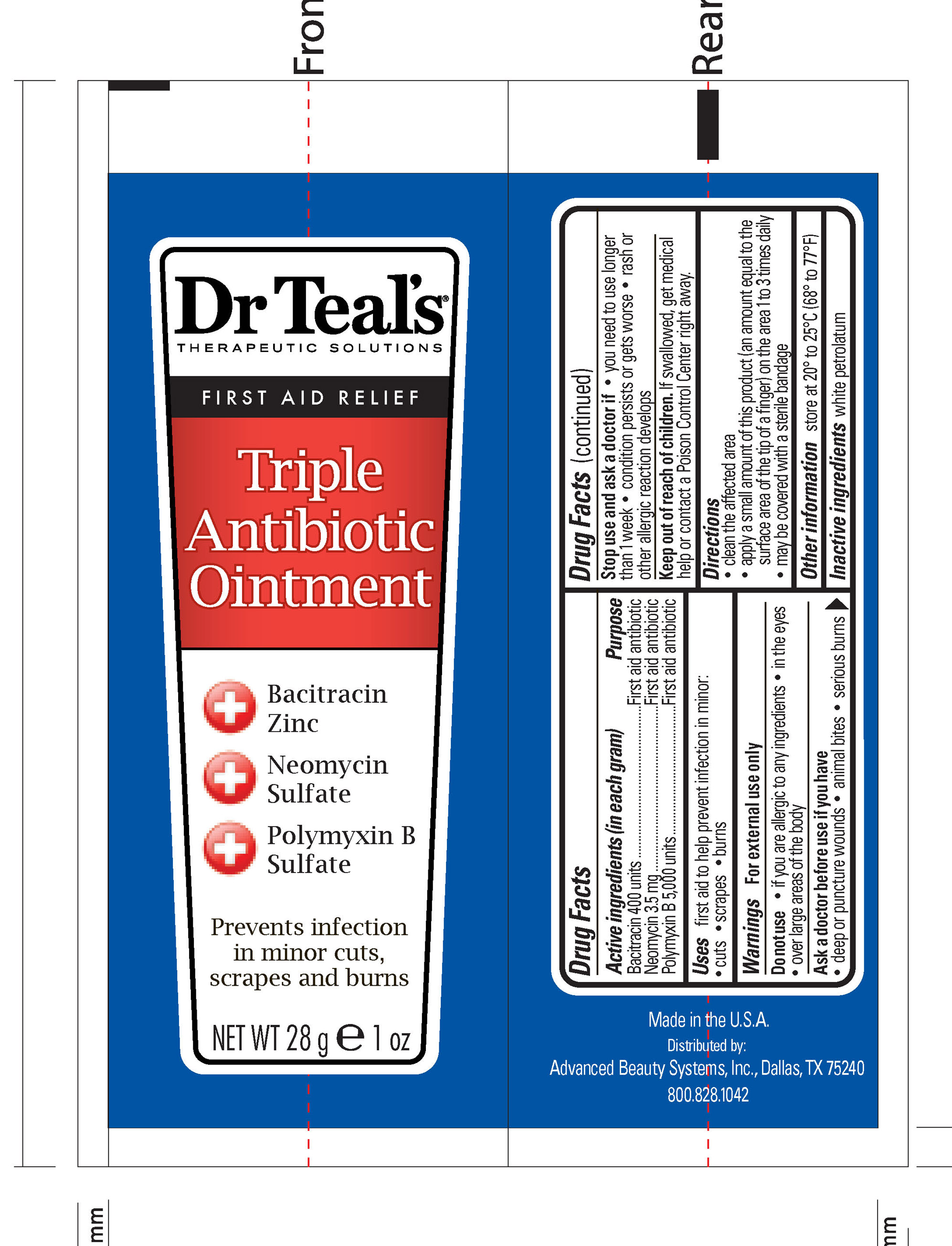 DRUG LABEL: 
                           
NDC: 51345-106 | Form: OINTMENT
Manufacturer: Advanced Beauty Systems, Inc.
Category: otc | Type: HUMAN OTC DRUG LABEL
Date: 20120810

ACTIVE INGREDIENTS: BACITRACIN 400 U/28 g; NEOMYCIN 3.5 mg/28 g; POLYMYXIN B 5000 U/28 g
INACTIVE INGREDIENTS: PETROLATUM

Dr Teals Tiple Antibiotic ointment

Active Ingredients (in each gram) Purpose

Bacitracin 400 units First aid antibiotic

Neomycin 3.5mg First aid antibiotic

Polymyxin B 5,000 units First aid antibiotic

PURPOSE

Uses first aid to help prevent infection in minor -cuts -scrapes -burns

Keep out of reach of children. If swallowed, get medical help or contact a Poison Control Center right away.

Stop use and ask a doctor if

-you need to use longer than 1 week

-condition persists or gets worse

-rash or other allergic reaction develop

Warnings For external use only

Do not use -if you are allergic to any ingredients -in the eyes -over large areas of the body

Ask a doctor before use if you have -deep or puncture wounds -animal bites -serious burns

Directions

-clean the affected area

-apply a small amount of this product (an amount equal to the surface area of the tip of a finger) on the area 1 to 3 times daily

-may be covered with a sterile bandage

Inactive Ingredient: White Petrolatum

PACKAGE LABEL

Dr Teals

Therapeutic Solutions

First aid relief

Triple Antibiotic Ointment

Bacitracin Zinc

Neomycin Sulfate

Polymyxin B Sulfate

Prevents infection in minor cuts, scrapes, and burns

Net Wt 28 g 1oz